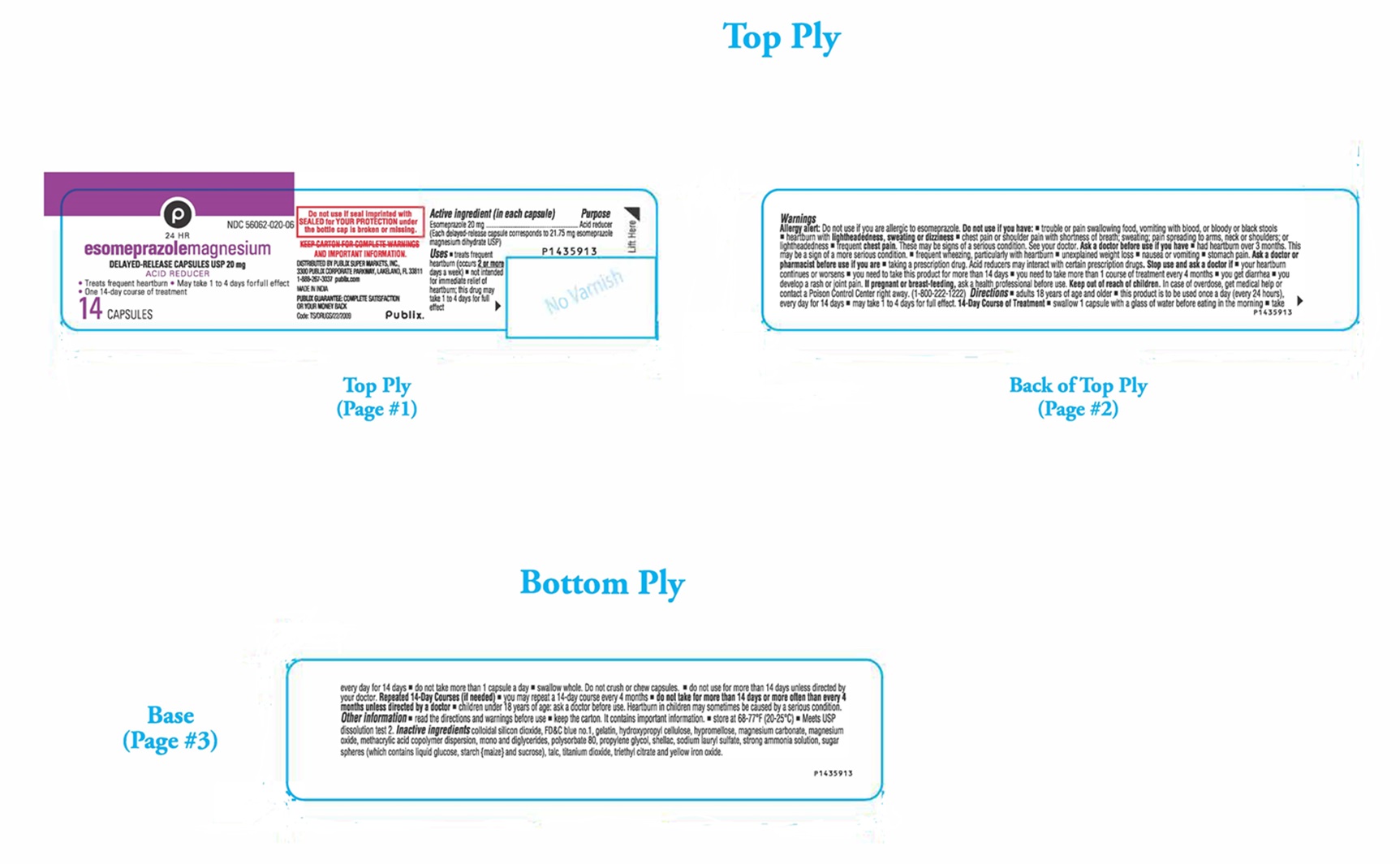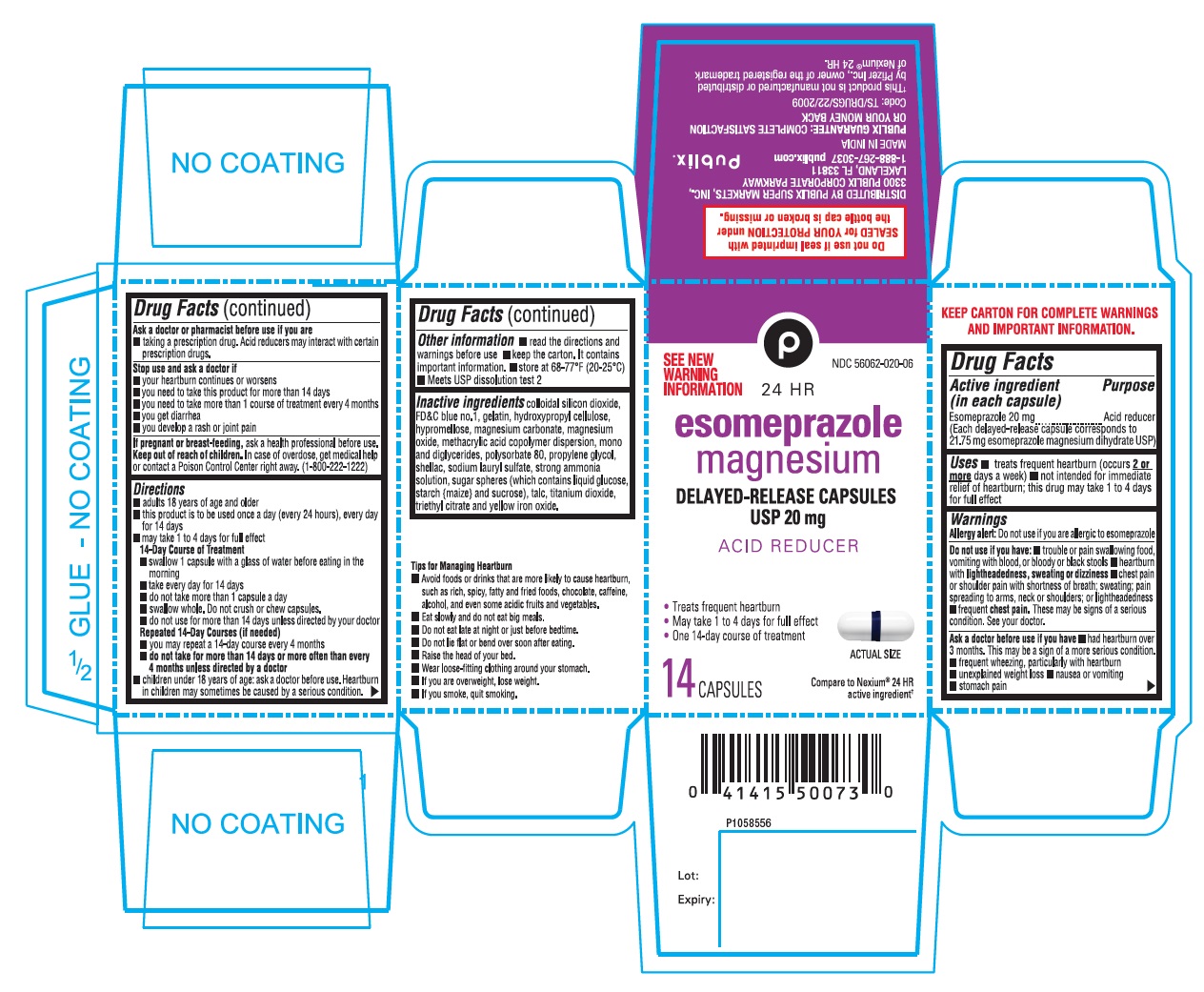 DRUG LABEL: Esomeprazole Magnesium
NDC: 56062-020 | Form: CAPSULE, DELAYED RELEASE
Manufacturer: Publix
Category: otc | Type: Human OTC Drug Label
Date: 20250221

ACTIVE INGREDIENTS: ESOMEPRAZOLE MAGNESIUM DIHYDRATE 20 mg/1 1
INACTIVE INGREDIENTS: SILICON DIOXIDE; FD&C BLUE NO. 1; GELATIN, UNSPECIFIED; HYDROXYPROPYL CELLULOSE, UNSPECIFIED; HYPROMELLOSE, UNSPECIFIED; MAGNESIUM CARBONATE; MAGNESIUM OXIDE; METHACRYLIC ACID - ETHYL ACRYLATE COPOLYMER (1:1) TYPE A; GLYCERYL MONOSTEARATE; POLYSORBATE 80; PROPYLENE GLYCOL; SHELLAC; SODIUM LAURYL SULFATE; AMMONIA; DEXTROSE, UNSPECIFIED FORM; STARCH, CORN; SUCROSE; TALC; TITANIUM DIOXIDE; TRIETHYL CITRATE; FERRIC OXIDE YELLOW

Esomeprazole Magnesium Delayed-Release Capsules USP 20 mg

Drug Facts

Active ingredient (in each capsule)

Esomeprazole 20 mg
(Each delayed-release capsule corresponds to 21.75 mg esomeprazole magnesium dihydrate USP)

Purpose

Acid reducer

Uses

- treats frequent heartburn (occurs 2 or more days a week)
- not intended for immediate relief of heartburn; this drug may take 1 to 4 days for full effect

Warnings

Allergy alert: Do not use if you are allergic to esomeprazole

Do not use if you have:

- trouble or pain swallowing food, vomiting with blood, or bloody or black stools
- heartburn with lightheadedness, sweating or dizziness
- chest pain or shoulder pain with shortness of breath; sweating; pain spreading to arms, neck or shoulders; or lightheadedness
- frequent chest pain

These may be signs of a serious condition. See your doctor.

Ask a doctor before use if you have

- had heartburn over 3 months. This may be a sign of a more serious condition.
- frequent wheezing, particularly with heartburn
- unexplained weight loss
- nausea or vomiting
- stomach pain

Ask a doctor or pharmacist before use if you are

- taking a prescription drug. Acid reducers may interact with certain prescription drugs.

Stop use and ask a doctor if

- your heartburn continues or worsens
- you need to take this product for more than 14 days
- you need to take more than 1 course of treatment every 4 months
- you get diarrhea
- you develop a rash or joint pain

If pregnant or breast-feeding, ask a health professional before use.

Keep out of reach of children.

In case of overdose, get medical help or contact a Poison Control Center right away (1-800-222-1222).

Directions

- adults 18 years of age and older
- this product is to be used once a day (every 24 hours), every day for 14 days
- may take 1 to 4 days for full effect

14-Day Course of Treatment

- swallow 1 capsule with a glass of water before eating in the morning
- take every day for 14 days
- do not take more than 1 capsule a day
- swallow whole. Do not crush or chew capsules.
- do not use for more than 14 days unless directed by your doctor

Repeated 14-Day Courses (if needed)

- you may repeat a 14-day course every 4 months
- do not take for more than 14 days or more often than every 4 months unless directed by a doctor
- children under 18 years of age: ask a doctor before use. Heartburn in children may sometimes be caused by a serious condition.

Other information

- read the directions and warnings before use
- keep the carton. It contains important information.
- store at 68-77°F (20-25°C)
- Meets USP dissolution test 2

Inactive ingredients

colloidal silicon dioxide, FD&C blue no.1, gelatin, hydroxypropyl cellulose, hypromellose, magnesium carbonate, magnesium oxide, methacrylic acid copolymer dispersion, mono and di glycerides, polysorbate 80, propylene glycol, shellac, sodium lauryl sulfate, strong ammonia solution, sugar spheres (which contains liquid glucose, starch {maize} and sucrose), talc, titanium dioxide, triethyl citrate and yellow iron oxide.

DISTRIBUTED BY PUBLIX SUPER MARKETS, INC.,
3300 PUBLIX CORPORATE PARKWAY
LAKEAND, FL 33811
1-888-267-3037 publix.com
MADE IN INDIA
PUBLIX GURANTEE: COMPLETE SATISFACTION
OR YOUR MONEY BACK
Code: TS/DRUGS/22/2009

PACKAGE LABEL-PRINCIPAL DISPLAY PANEL - 20 mg (14 Capsules Container Label)

24 HR NDC 56062-020-06
esomeprazole magnesium
DELAYED-RELEASE CAPSULES USP 20 mg
ACID REDUCER
• Treats frequent heartburn • May take 1 to 4 days for full effect
• One 14-day course of treatment
14 CAPSULES

PACKAGE LABEL-PRINCIPAL DISPLAY PANEL - 20 mg (14 Capsules Container Carton Label)

SEE NEW NDC 58602-020-06
WARNINGS 24 HR
INFORMATION
esomeprazole
magnesium
DELAYED-RELEASE CAPSULES
USP 20 mg
ACID REDUCER
•Treats frequent heartburn

•May take 1 to 4 days for full effect
•One 14-day course of treatment
ACTUAL SIZE
14 CAPSULES
Compare to Nexium® 24 HR
active ingredient†